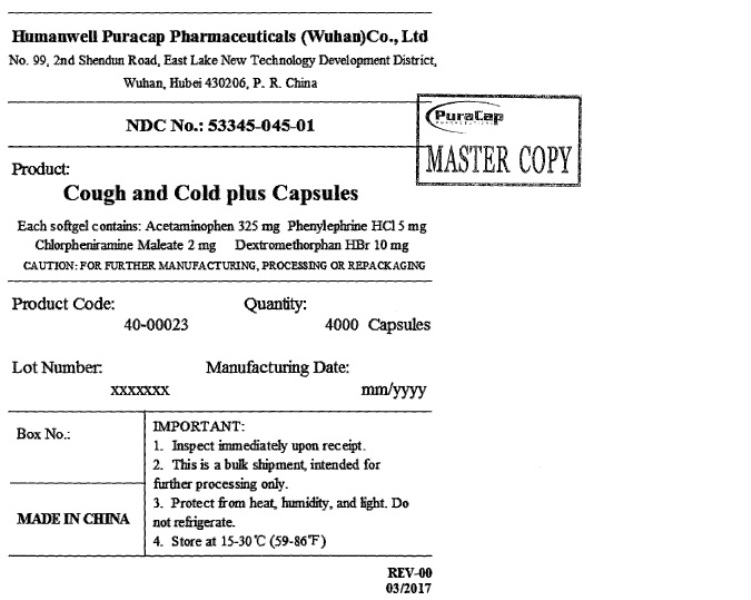 DRUG LABEL: Cough and Cold plus
NDC: 53345-045 | Form: CAPSULE, LIQUID FILLED
Manufacturer: Humanwell PuraCap Pharmaceutical (Wuhan) Co., Ltd
Category: otc | Type: HUMAN OTC DRUG LABEL
Date: 20241125

ACTIVE INGREDIENTS: ACETAMINOPHEN 325 mg/1 1; PHENYLEPHRINE HYDROCHLORIDE 5 mg/1 1; CHLORPHENIRAMINE MALEATE 2 mg/1 1; DEXTROMETHORPHAN HYDROBROMIDE 10 mg/1 1
INACTIVE INGREDIENTS: BUTYLATED HYDROXYANISOLE; D&C RED NO. 33; FD&C BLUE NO. 1; GELATIN; GLYCERIN; POLYETHYLENE GLYCOL, UNSPECIFIED; POVIDONE; PROPYLENE GLYCOL; SORBITAN; SORBITOL; WATER

Cough and Cold plus

Active ingredients (in each softgel)

Acetaminophen 325 mg

Chlorpheniramine maleate 2 mg

Dextromethorphan hydrobromide 10 mg

Phenylephrine hydrochloride 5 mg

Purpose

Pain reliever/fever reducer

Antihistamine

Cough suppressant

Nasal decongestant

Uses

- temporarily relieves these symptoms due to a cold or flu:
- minor aches and pains
- headache
- nasal and sinus congestion
- cough
- runny nose
- sneezing
- sore throat
- temporarily reduces fever

Warnings

Liver warning

This product contains acetaminophen. Severe liver damage may occur if you take

- more than 10 softgels in 24 hours, which is the maximum daily amount for this product
- with other drugs containing acetaminophen
- 3 or more alcoholic drinks every day while using this product

Allergy alert

Acetaminophen may cause severe skin reactions. Symptoms may include:

- skin reddening
- blisters
- rash

If a skin reaction occurs, stop use and seek medical help right away.

Sore throat warning

If sore throat is severe, persists for more than 2 days, is accompanied or followed by fever, headache, rash, nausea, or vomiting, consult a doctor promptly.

Do not use to sedate children.

Do not use

- with any other drug containing acetaminophen (prescription or nonprescription). If you are not sure whether a drug contains acetaminophen, ask a doctor or pharmacist.
- if you are now taking a prescription monoamine oxidase inhibitor (MAOI) (certain drugs for depression, psychiatric or emotional conditions, or Parkinson's disease), or for 2 weeks after stopping the MAOI drug. If you do not know if your prescription drug contains an MAOI, ask a doctor or pharmacist before taking this product.
- if you have ever had an allergic reaction to this product or any of its ingredients
- in children under 12 years of age

Ask a doctor before use if you have

- liver disease
- heart disease
- high blood pressure
- thyroid disease
- diabetes
- glaucoma
- cough with excessive phlegm (mucus)
- a breathing problem such as emphysema or chronic bronchitis
- difficulty in urination due to enlargement of the prostate gland
- persistent or chronic cough such as occurs with smoking, asthma, or emphysema

Ask a doctor or pharmacist before use if you are

- taking the blood thinning drug warfarin
- taking sedatives or tranquilizers

When using this product

- do not exceed recommended dosage
- may cause marked drowsiness
- avoid alcoholic drinks
- alcohol, sedatives, and tranquilizers may increase drowsiness
- be careful when driving a motor vehicle or operating machinery
- excitability may occur, especially in children

Stop use and ask a doctor if

- pain, cough, or nasal congestion gets worse or lasts more than 7 days
- fever gets worse or lasts more than 3 days
- redness or swelling is present
- new symptoms occur
- cough comes back or occurs with rash or headache that lasts.

These could be signs of a serious condition.

- nervousness, dizziness, or sleeplessness occurs

PREGNANCY OR BREAST FEEDING

If pregnant or breast-feeding, ask a health professional before use.

Keep out of reach of children. In case of overdose, get medical help or contact a Poison Control Center right away. Quick medical attention is critical for adults as well as for children even if you do not notice any signs or symptoms.

Directions

- do not take more than the recommended dose
- adults and children 12 years and over: take 2 softgels with water every 4 hours. Do not exceed 10 softgels in 24 hours or as directed by a doctor.
- children under 12 years: do not use

Other information

- Store at room temperature 15°-30°C (59°F-86°F) and avoid excessive heat.

Inactive ingredients

Butylated Hydroxyanisole (BHA), D&C red #33, FD&C blue #1, gelatin, glycerin, polyethylene glycol, povidone, propylene glycol, purified water, sorbitol sorbitan solution, white ink

Questions or commonts

Call toll free: 1-855-215-8180

PRINCIPAL DISPLAY PANEL - Shipping Label

Cough and Cold plus Capsules

Each softgel contains: Acetaminophen 325 mg Phenylephrine HCl 5 mg

Chlorpheniramine Maleate 2 mg Dextromethorphan HBr 10 mg

Quantity: 4000 Capsules

NDC No.:53345-045-01

MADE IN CHINA

IMPORTANT:

1. Inspect immediately upon receipt.
2. This is a bulk shipment, intended for further processing only.
3. Protect from heat, humidity, and light. Do not refrigerate.
4. 4.Store at 15-30°C (59-86)°F